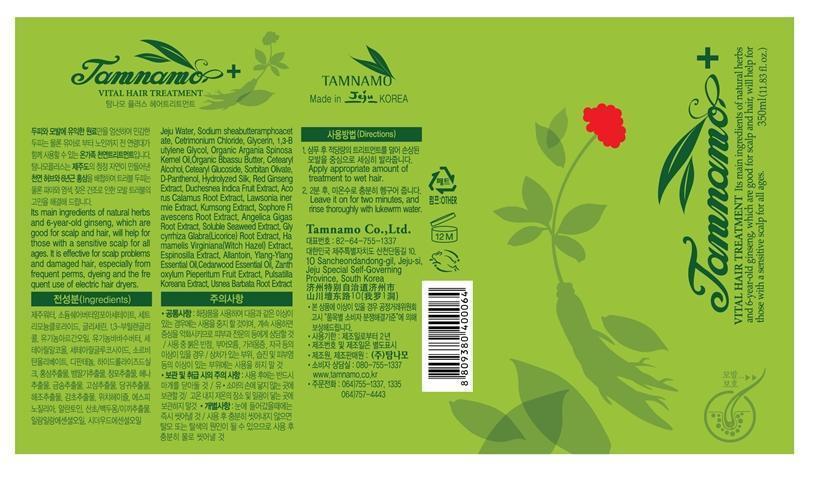 DRUG LABEL: Tamnamo Vital Hair Treatment
NDC: 60344-7001 | Form: LIQUID
Manufacturer: Tamnamo Co., Ltd
Category: otc | Type: HUMAN OTC DRUG LABEL
Date: 20140308

ACTIVE INGREDIENTS: ALLANTOIN 0.002 g/1 mL
INACTIVE INGREDIENTS: CETOSTEARYL ALCOHOL; GLYCERIN; DEXPANTHENOL; ANGELICA GIGAS ROOT; GLYCYRRHIZA GLABRA

Drug Facts

ACTIVE INGREDIENT

allantoin

INACTIVE INGREDIENT

Jeju Water, Sodium sheabutteramphoacetate, Cetrimonium Chloride, Glycerin, 1,3-Butylene Glycol, Argania Spinosa Kernel Oil, Organic Bbassu Butter, Cetearyl Alcohol, Cetearyl Glucoside, Sorbitan Olivate, D-Panthenol, Hydrolyzed Silk, Red Ginseng Extract, Duchesnea Indica Fruit Extract, Acorus Calamus Root Extract, Lawsonia inermie Extract, Kumsong Extract, Sophore Flavescens Root Extract, Angelica Gigas Root Extract, Soluble Seaweed Extract, Glycyrrhiza Glabra (Licorice) Root Extract, Hamamelis Virginiana (Witch Hazel) Extract, Espinosilla Extract, Allantoin, Ylang-Ylang Essential Oil, Cedarwood Essential Oil, Zanthoxylum Pieperitum Fruit Extract,

Pulsatilla Koreana Extract, Usnea Barbata Root Extract

PURPOSE

supplying moisture and nutrient to scalp and hair

keep out of reach of the children

INDICATIONS AND USAGE

apply appropriate amount of treatment to wet hair
leave it on for two minutes, and rinse thoroughly with lukewarm water

stop use if irritation occurs
avoid contact with eyes

DOSAGE AND ADMINISTRATION

for external use only